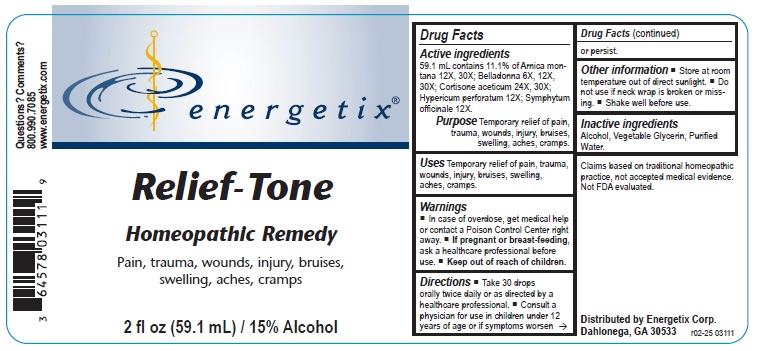 DRUG LABEL: Relief-Tone
NDC: 64578-0092 | Form: LIQUID
Manufacturer: Energetix Corporation
Category: homeopathic | Type: HUMAN OTC DRUG LABEL
Date: 20250711

ACTIVE INGREDIENTS: ARNICA MONTANA 12 [hp_X]/1 mL; ATROPA BELLADONNA 6 [hp_X]/1 mL; CORTISONE ACETATE 24 [hp_X]/1 mL; HYPERICUM PERFORATUM 12 [hp_X]/1 mL; COMFREY ROOT 12 [hp_X]/1 mL
INACTIVE INGREDIENTS: WATER; GLYCERIN; ALCOHOL

Relief-Tone

ACTIVE INGREDIENT

Active ingredients 59.1 mL contains 11.1% of Arnica montana 12X, 30X; Belladonna 6X, 12X, 30X; Cortisone aceticum 24X, 30X; Hypericum perforatum 12X; Symphytum officinale 12X.

Claims based on traditional homeopathic practice, not accepted medical evidence. Not FDA evaluated,

Uses

Temporary relief of pain, trauma, wounds, injury, bruises, swelling, aches, cramps.

Warnings

- In case of overdose, get medical help or contact a Poison Control Center right away.
- If pregnant or breast-feeding, ask a healthcare professional before use.

- Keep out of reach of children.

Directions

- Take 30 drops orally twice daily or as directed by a healthcare professional.
- Consult a physician for use in children under 12 years of age if symptoms worsen or persist.

Other information

- Store at room temperature out of direct sunlight.
- Do not use if neck wrap is broken or missing.
- Shake well before use.

Inactive ingredients

Alcohol, Vegetable Glycerin, Purified Water.

QUESTIONS

Distributed by Energetix Corp.

Dahlonega, GA 30533

Questions? Comments?

800.990.7085

www.energetix.com

PACKAGE LABEL

energetix

Relief-Tone

Homeopathic Remedy

Pain, trauma, wounds, injury, bruises, swelling, aches, cramps.

2 fl oz (59.1 mL) / 15% Alcohol

PURPOSE

Purpose Temporary relief of pain, trauma, wounds, injury, bruises, sweliing, aches, cramps.